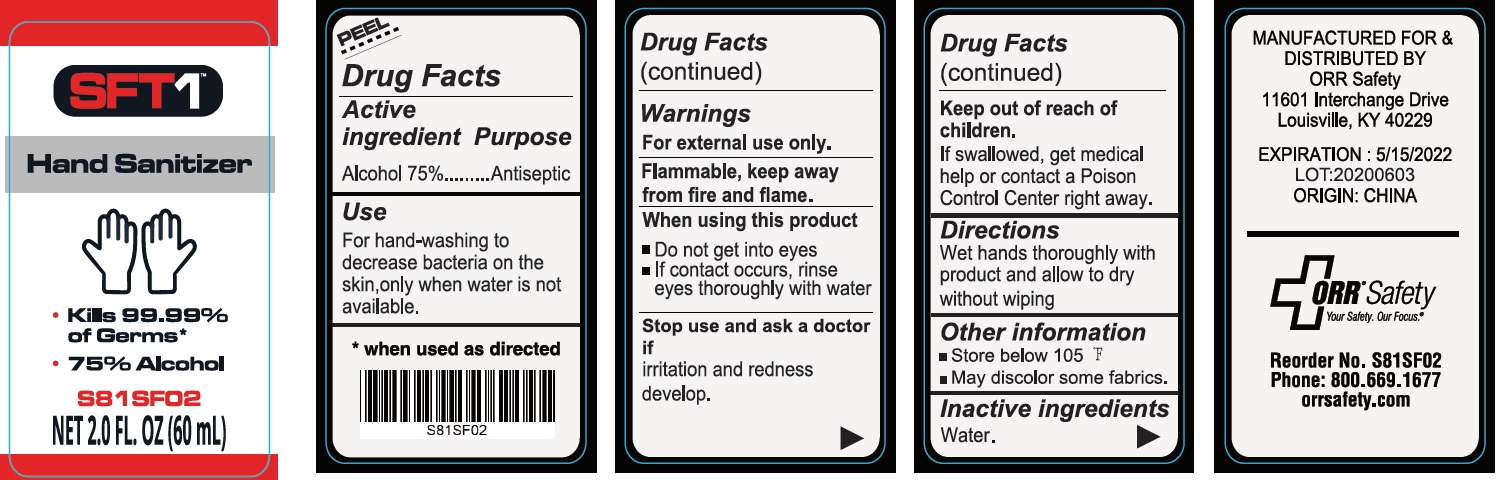 DRUG LABEL: Hand Sanitizer
NDC: 79401-000 | Form: SPRAY
Manufacturer: ORR Safety Corporation
Category: otc | Type: HUMAN OTC DRUG LABEL
Date: 20231026

ACTIVE INGREDIENTS: ALCOHOL 0.75 mL/1 mL
INACTIVE INGREDIENTS: WATER

Hand Sanitizer Spray

Active ingredient

Alcohol 75%

Purpose

Antiseptic

Use

For hand-washing to decrease bacteria on the skin, only when water is not available.

Warnings

For external use only.

Flammable, keep away from fire and flame.

When using this product

- do not get into eyes.
- if contact occurs, rinse eyes thoroughly with water

Stop use and ask a doctor if

irritation and redness develop.

Keep out of reach of children.

if swallowed, get medical help or contact a Poison Control Center right away.

Directions

Wet hands thoroughly with product and allow to dry without wiping

Other information

- Store Below 105 °F
- May discolor some fabrics

Inactive ingredients

Water.